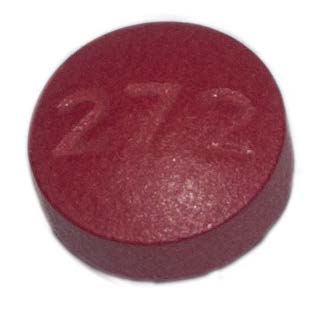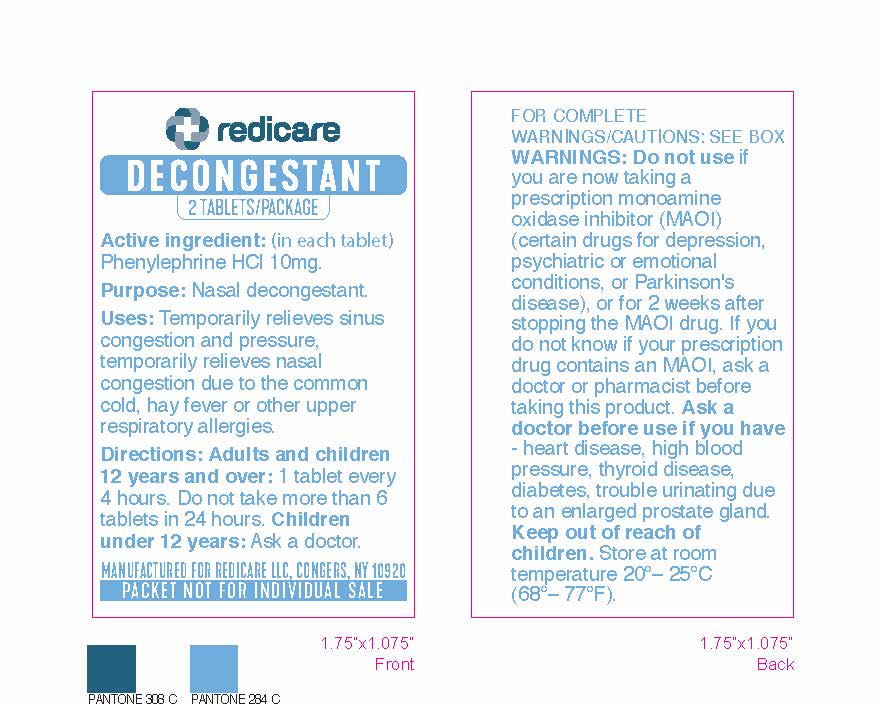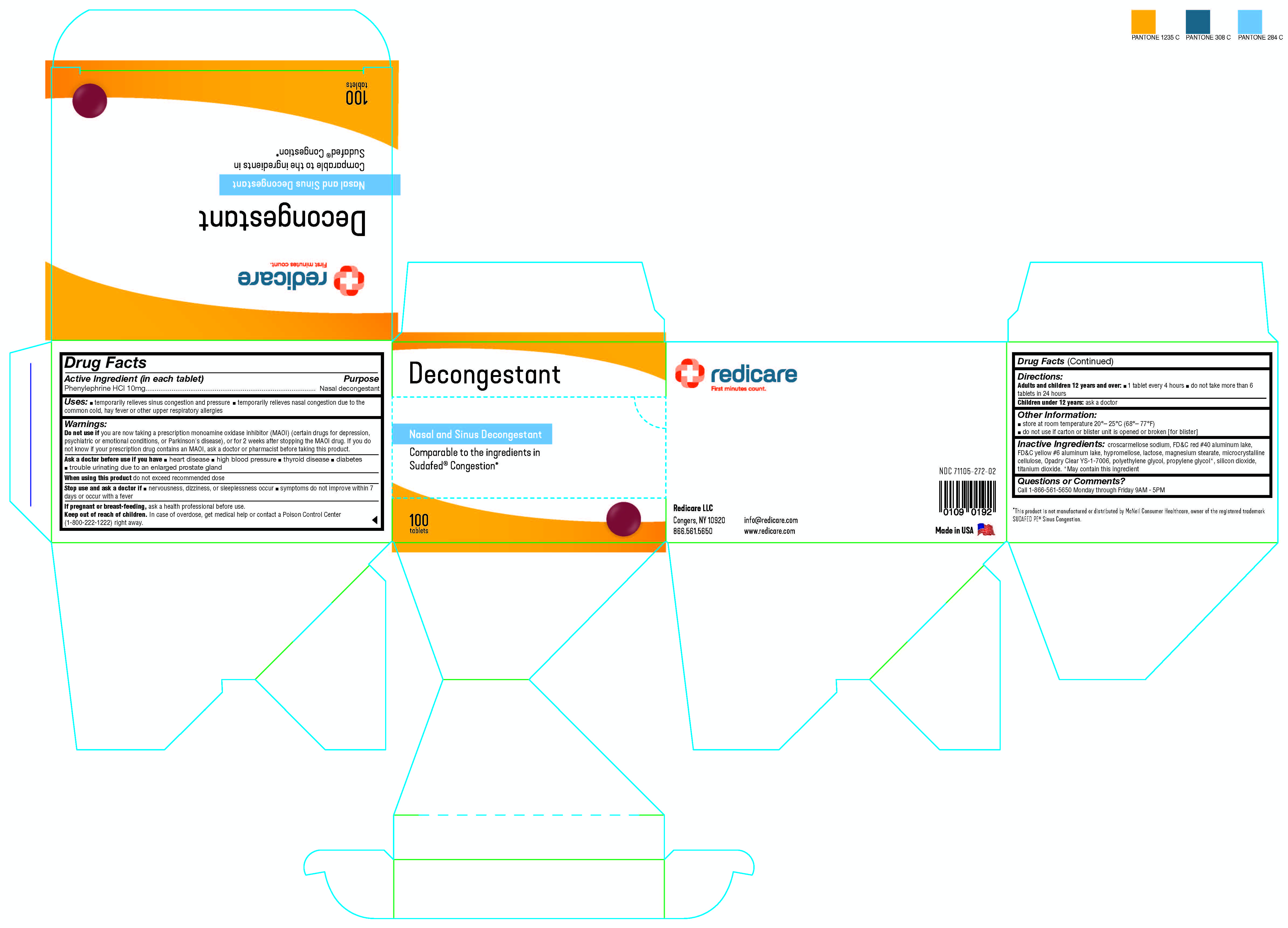 DRUG LABEL: Redicare Nasal and Sinus Decongestant
NDC: 71105-272 | Form: TABLET
Manufacturer: Redicare LLC
Category: otc | Type: HUMAN OTC DRUG LABEL
Date: 20250304

ACTIVE INGREDIENTS: PHENYLEPHRINE HYDROCHLORIDE 10 mg/1 1
INACTIVE INGREDIENTS: SILICON DIOXIDE; FD&C RED NO. 40; PROPYLENE GLYCOL; CROSCARMELLOSE SODIUM; CELLULOSE, MICROCRYSTALLINE; HYPROMELLOSES; FD&C YELLOW NO. 6; MAGNESIUM STEARATE; TITANIUM DIOXIDE; POLYETHYLENE GLYCOL, UNSPECIFIED; LACTOSE, UNSPECIFIED FORM

Redicare Nasal and Sinus Decongestant

Active Ingredient (in each tablet)

Phenylephrine HCl 10mg

Purpose

Nasal decongestant

Uses:

■ temporarily relieves sinus congestion and pressure ■ temporarily relieves nasal congestion due to the common cold, hay fever or other upper respiratory allergies

Warnings:

Do not use if

you are now taking a prescription monoamine oxidase inhibitor (MAOI) (certain drugs for depression, psychiatric or emotional conditions, or Parkinson's disease), or for 2 weeks after stopping the MAOI drug. If you do not know if your prescription drug contains an MAOI, ask a doctor or pharmacist before taking this product.

Ask a doctor before use if you have

■ heart disease ■ high blood pressure ■ thyroid disease ■ diabetes ■ trouble urinating due to an enlarged prostate gland

When using this product

do not exceed recommended dose

Stop use and ask a doctor if

■ nervousness, dizziness, or sleeplessness occur ■ symptoms do not improve within 7 days or occur with a fever

If pregnant or breast-feeding,

ask a health professional before use.

Keep out of reach of children.

In case of overdose, get medical help or contact a Poison Control Center (1-800-222-1222) right away.

Directions:

Adults and children 12 years and over: ■ 1 tablet every 4 hours ■ do not take more than 6 tablets in 24 hours
Children under 12 years: ask a doctor

Other Information:

■ store at room temperature 20°– 25°C (68°– 77°F)
■ do not use if carton or blister unit is opened or broken [for blister]

Inactive Ingredients:

croscarmellose sodium, FD&C red #40 aluminum lake, FD&C yellow #6 aluminum lake, hypromellose, lactose, magnesium stearate, microcrystalline cellulose, Opadry Clear YS-1-7006, polyethylene glycol, propylene glycol*, silicon dioxide, titanium dioxide. *May contain this ingredient

Questions or Comments?

Call 1-866-561-5650 Monday through Friday 9AM - 5PM